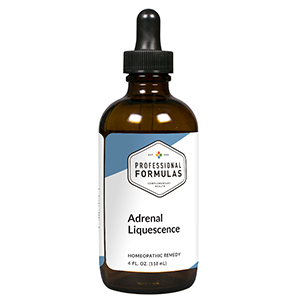 DRUG LABEL: Adrenal Liquescence
NDC: 63083-3001 | Form: LIQUID
Manufacturer: Professional Complementary Health Formulas
Category: homeopathic | Type: HUMAN OTC DRUG LABEL
Date: 20190815

ACTIVE INGREDIENTS: GLYCYRRHIZA GLABRA 1 [hp_X]/118 mL; BEE POLLEN 2 [hp_X]/118 mL; PAULLINIA CUPANA SEED 3 [hp_X]/118 mL; ROSA CANINA FRUIT 3 [hp_X]/118 mL; ASIAN GINSENG 3 [hp_X]/118 mL; SUS SCROFA ADRENAL GLAND 6 [hp_X]/118 mL; CORTICOTROPIN 6 [hp_X]/118 mL; EPHEDRA DISTACHYA FLOWERING TWIG 6 [hp_X]/118 mL; ZINC 6 [hp_X]/118 mL; EPINEPHRINE 12 [hp_X]/118 mL; SODIUM CHLORIDE 12 [hp_X]/118 mL
INACTIVE INGREDIENTS: ALCOHOL; WATER

T1

ACTIVE INGREDIENTS

Glycyrrhiza glabra 1X
Bee pollen 2X
Paullinia sorbilis 3X
Rosa canina 3X
Panax ginseng (Chinese) 3X, 6X
Adrenal 6X
Adrenocorticotrophin (ACTH) 6X
Ephedra vulgaris 6X
Zincum metallicum 6X
Adrenalinum 12X
Natrum muriaticum 12X

QUESTIONS

Professional Formulas

PO Box 2034 Lake Oswego, OR 97035

INDICATIONS

For the temporary relief of lethargy, lack of energy, sadness, anxiousness, or decreased ability to handle stress.*

PURPOSE

*Claims based on traditional homeopathic practice, not accepted medical evidence. Not FDA evaluated.

WARNINGS

In case of overdose, get medical help or contact a poison control center right away.

Keep out of the reach of children.

PREGNANCY OR BREAST FEEDING

If pregnant or breastfeeding, ask a healthcare professional before use.

DIRECTIONS

Place drops under tongue 30 minutes before/after meals. Adults and children 12 years and over: Take one full dropper up to 2 times per day. Consult a physician for use in children under 12 years of age.

OTHER INFORMATION

Tamper resistant. If seal is broken, do not use. After opening, close container tightly and store at room temperature away from heat.

INACTIVE INGREDIENTS

20% ethanol, purified water.

LABEL

Est 1985

Professional Formulas

Complementary Health

Adrenal Liquescence

Homeopathic Remedy

4 FL. OZ. (118 mL)